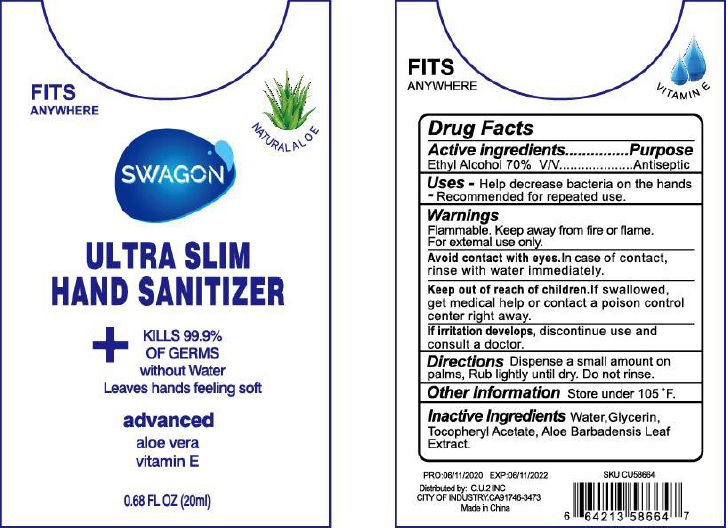 DRUG LABEL: Swagon Ultra Slim Hand Sanitizer
NDC: 54096-102 | Form: GEL
Manufacturer: Dongyang Caiyi Cosmetics Co., Ltd.
Category: otc | Type: HUMAN OTC DRUG LABEL
Date: 20200723

ACTIVE INGREDIENTS: alcohol 70 mL/100 mL
INACTIVE INGREDIENTS: WATER; .ALPHA.-TOCOPHEROL ACETATE, D-; GLYCERIN; ALOE VERA LEAF

Drug facts

ACTIVE INGREDIENT

Ethyl Alcohol .................... 70% v/v

PURPOSE

Antiseptic

KEEP OUT OF REACH OF CHILDREN

If swallowed, get medical help or contact a Poison Control Center right away.

INDICATIONS AND USAGE

- Help decrease bacteria on the hands
- recommended for repeated use.

WARNINGS

For external use only: hands
Flammable. Keep away from heat or flame.

When using this products

Avoid contact with eyes, in case of contact, rinse with water immediately.

Stop using and ask a doctor if irritation develops.

Other information

- store under 105℉

DOSAGE AND ADMINISTRATION

Dispense a small amount on palms, rub lightly until dry. Do not rinse.

INACTIVE INGREDIENT

Water (aqua), Glycerin, Tocopheryl Acetate, Aloe Barbadensis Leaf Extract